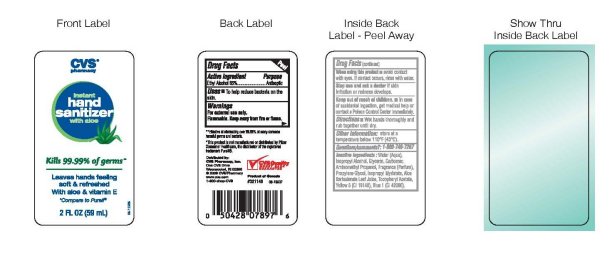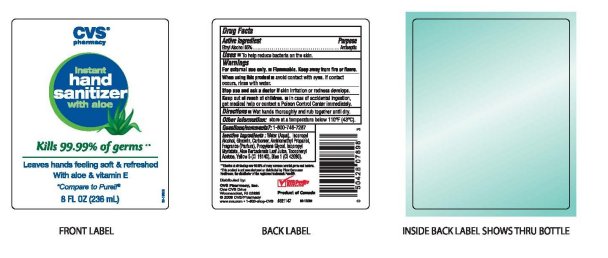 DRUG LABEL: CVS Pharmacy Instant Hand Sanitizer With Aloe And Vitamin E
NDC: 59779-210 | Form: GEL
Manufacturer: CVS Pharmacy
Category: otc | Type: HUMAN OTC DRUG LABEL
Date: 20100216

ACTIVE INGREDIENTS: ALCOHOL 65 mL/100 mL
INACTIVE INGREDIENTS: WATER; ISOPROPYL ALCOHOL; GLYCERIN; CARBOMER HOMOPOLYMER TYPE C; PROPYLENE GLYCOL; ISOPROPYL MYRISTATE; ALOE VERA LEAF; ALPHA-TOCOPHEROL ACETATE; FD&C YELLOW NO. 5; FD&C BLUE NO. 1

CVS Instant Hand Sanitizer With Aloe & Vitamin E

Active Ingredient Purpose

Ethyl Alchohol 65 Percent Antiseptic

Uses

To help reduce bacteria on the skin.

Warnings

For external use only.

Flammable. Keep away from fire or flame.

When using this product

Avoid contact with eyes.

If contact occurs, rinse with water.

Stop use and ask a doctor if skin irritation or redness develops.

Keep out of reach of children.

In case of accidental ingestion, get medical help or contact a Poison Control Center immediately.

Directions

Wet hands thoroughly and rub together until dry.

Other information:

Store at a temperature below 110 degrees F (43 degrees C)

Questions Comments ? : 1-800-746-7287

INACTIVE INGREDIENT

Inactive ingredients: Water aqua, Isopropyl Alcohol, Glycerin, Carbomer, Aminomethyl Propanol, Fragrance Parfum,

Propylene Glycol, Isopropyl Myristate, Aloe Barbadensis Leaf Juice, Tocopheryl Acetate, Yellow 5 CI 19140, Blue 1 CI 42090

DESCRIPTION

Effective at eliminating over 99.99 percent of many common harmful germs and bacteria.

This product is not manufactured or distributed by Pfizer Consumer Healthcare, the distributor of the registered trademark Purell.
Distributed by
CVS Pharmacy, Inc.
One CVS Drive
Woonsocket, RI 02895
2009 CVS Pharmacy
www.cvs.com
1-800-shop-cvs
CVS Quality
Money Back Guarantee
Product of Canada

PACKAGE LABEL

CVS Pharmacy

Instant Hand Sanitizer

with aloe

Kills 99.99 percent of germs

Leaves hands feeling soft and refreshed

With aloe and vitamin E

Compare to Purell

2 FL OZ 59 ml

8 Fl OZ 236 ml